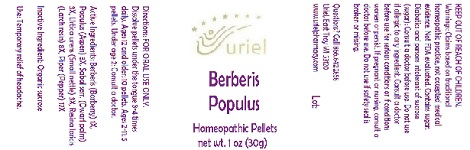 DRUG LABEL: Berberis Populus
NDC: 48951-2048 | Form: PELLET
Manufacturer: Uriel Pharmacy Inc.
Category: homeopathic | Type: HUMAN OTC DRUG LABEL
Date: 20180531

ACTIVE INGREDIENTS: BERBERIS VULGARIS ROOT BARK 1 [hp_X]/1 1; POPULUS TREMULA WHOLE 3 [hp_X]/1 1; SAW PALMETTO 3 [hp_X]/1 1; URTICA URENS 3 [hp_X]/1 1; LARIX DECIDUA RESIN 8 [hp_X]/1 1; BLACK PEPPER 17 [hp_X]/1 1
INACTIVE INGREDIENTS: SUCROSE

Berberis Populus

INDICATIONS AND USAGE

Directions: FOR ORAL USE ONLY.

DOSAGE AND ADMINISTRATION

Dissolve pellets under the tongue 3-4 times daily. Ages 12 and older: 10 pellets. Ages 2-11: 5 pellets. Under age 2: Consult a doctor.

ACTIVE INGREDIENT

Active Ingredients: Berberis (Barberry) 1X, Populus (Aspen) 3X, Sabal serr. (Dwarf palm) 3X, Urtica urens (Small nettle) 3X, Resina laricis (Larch resin) 8X, Piper (Pepper) 17X

Inactive Ingredient: Organic sucrose

PURPOSE

Use: Temporary relief of headache.

KEEP OUT OF REACH OF CHILDREN.

WARNINGS

Warnings: Claims based on traditional homeopathic practice, not accepted medical evidence. Not FDA evaluated. Contains sugar. Diabetics and persons intolerant of sucrose (sugar): Consult a doctor before use. Do not use if allergic to any ingredient. Consult a doctor before use for serious conditions or if conditions worsen or persist. If pregnant or nursing, consult a doctor before use. Do not use if safety seal is broken or missing.

QUESTIONS

Questions? Call 866.642.2858 Uriel, East Troy WI 53120 www.urielpharmacy.com